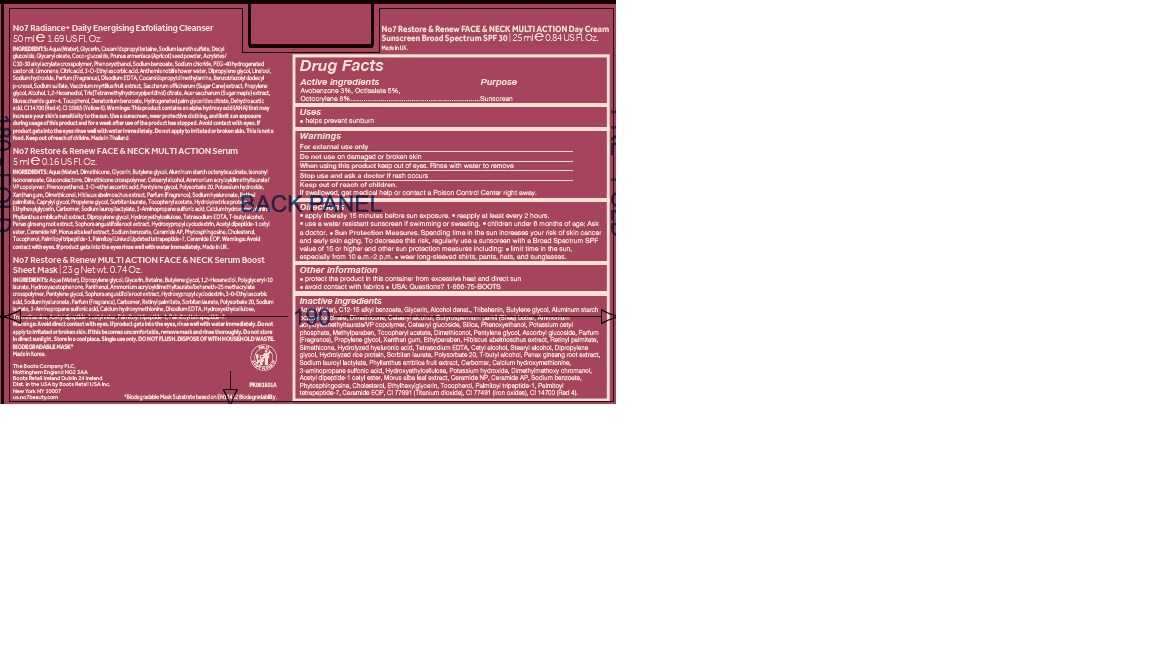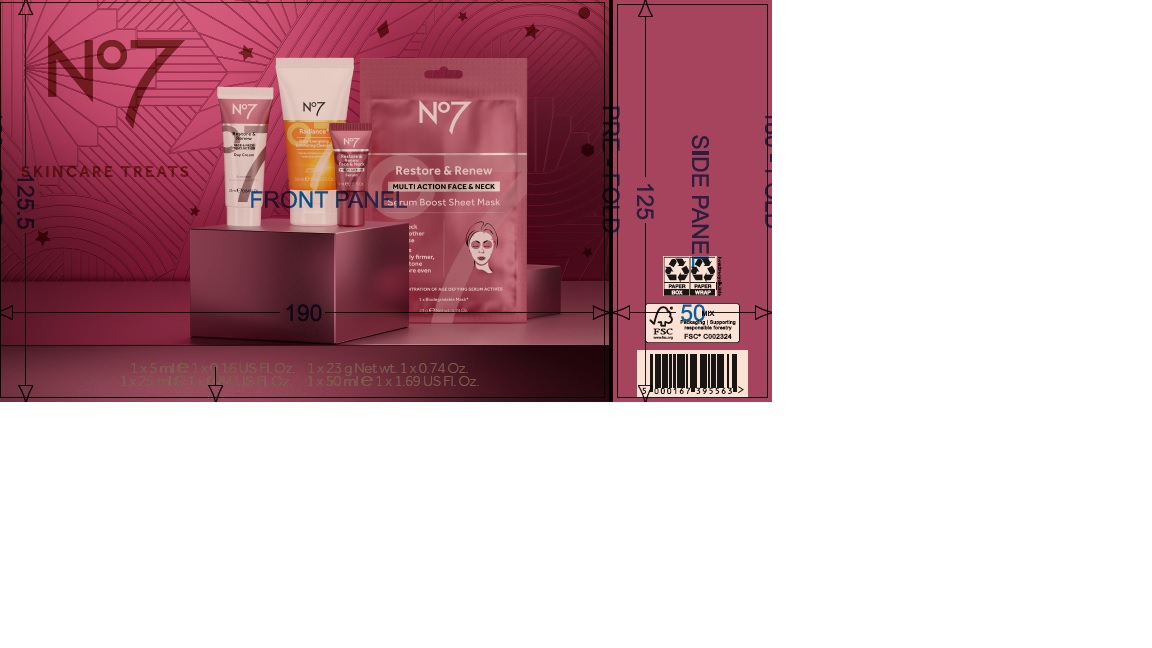 DRUG LABEL: No7 Restore and Renew Face and Neck Multi Action Day Cream Sunscreen Broad Spectrum SPF 30
NDC: 61589-9101 | Form: CREAM
Manufacturer: BCM Cosmetique SAS
Category: otc | Type: HUMAN OTC DRUG LABEL
Date: 20250801

ACTIVE INGREDIENTS: AVOBENZONE 1.5 g/25 mL; OCTOCRYLENE 4 g/25 mL; OCTISALATE 2.5 g/25 mL
INACTIVE INGREDIENTS: POLYSORBATE 20; POTASSIUM HYDROXIDE; MORUS ALBA LEAF; CERAMIDE 3; SODIUM BENZOATE; PHYTOSPHINGOSINE; CERAMIDE 6 II; CHOLESTEROL; ETHYLHEXYLGLYCERIN; TOCOPHEROL; CERAMIDE 1; TITANIUM DIOXIDE; BROWN IRON OXIDE; PALMITOYL TRIPEPTIDE-1; PALMITOYL TETRAPEPTIDE-7; CARBOXYPOLYMETHYLENE; ASIAN GINSENG; ACETYL TYROSYLARGININE CETYL ESTER; ALCOHOL; SILICON; ABELMOSCHUS MOSCHATUS WHOLE; HYALURONATE SODIUM; SORBITAN MONOLAURATE; WATER; GLYCERIN; ALUMINUM STARCH OCTENYLSUCCINATE; CETEARYL GLUCOSIDE; DIMETHICONE; TRIBEHENIN; AMMONIUM ACRYLOYLDIMETHYLTAURATE/VP COPOLYMER; PHENOXYETHANOL; SHEA BUTTER; POTASSIUM CETYL PHOSPHATE; BUTYLENE GLYCOL; DIMETHICONOL (100000 CST); PROPYLENE GLYCOL; METHYLPARABEN; ETHYLPARABEN; DIPROPYLENE GLYCOL; SODIUM LAUROYL LACTYLATE; PHYLLANTHUS EMBLICA FRUIT; XANTHAN GUM; HYDROXYETHYL CELLULOSE (100 MPA.S AT 2%); VITAMIN A PALMITATE; EDETATE SODIUM; TERT-BUTYL ALCOHOL

No7 Restore and Renew Face and Neck Multi Action Day Cream Sunscreen Broad Spectrum SPF 30

Carton Active Ingredients Section

Active ingredients

Avobenzone 3%

Octisalate 5%

Octocrylene 8%

Uses

helps prevent sunburn

Warnings

For external use only

Do not use on damaged or broken skin

When using this product keep out of eyes. Rinse with water to remove.

Warnings

For external use only

Do not use on damaged or broken skin

When using this product keep out of eyes. Rinse with water to remove.

Ask a doctor

Stop use and ask a doctor if rash occurs

Keep out of reach of children

If swallowed, get medical help or contact a Poison Control Center right away.

Directions

apply liberally 15 minutes before sun exposure.

reapply at least every 2 hours.

use a water resistant sunscreen if swimming or sweating.

children under 6 months of age: Ask a doctor.

Sun Protection Measures. Spending time in the sun increases your risk of skin cancer and early skin aging.

To decrease this risk, regularly use a sunscreen with a Broad Spectrum SPF value of 15 or higher and other sun protection measures including:

Limit time in the sun, especially from 10 a.m - 2 p.m.

wear long-sleeved shirts,pants,hats and sunglasses.

Directions

apply liberally 15 minutes before sun exposure.

reapply at least every 2 hours.

use a water resistant sunscreen if swimming or sweating.

children under 6 months of age: Ask a doctor.

Sun Protection Measures. Spending time in the sun increases your risk of skin cancer and early skin aging.

To decrease this risk, regularly use a sunscreen with a Broad Spectrum SPF value of 15 or higher and other sun protection measures including:

Limit time in the sun, especially from 10 a.m - 2 p.m.

wear long-sleeved shirts,pants,hats and sunglasses.

Storage

Other information

protect the product in this container from excessive heat and direct sun

avoid contact with fabrics

Inactive ingredients

Aqua (Water), C12-15 alkyl benzoate, Glycerin, Alcohol denat., Tribehenin, Butylene glycol, Aluminum starch octenylsuccinate, Dimethicone, Cetearyl alcohol, Cetearyl glucoside, Butyrospermum parkii (Shea) butter, Ammonium acryloydimethyltaurate/VP copolymer, Cetearyl glucoside, Silica, Phenoxyethanol, Potassium cetyl phosphate, Methylparaben, Parfum (Fragrance), Propylene glycol, Xanthan gum, Ethylparaben, Hibiscus abelmoschus extract, Retinyl palmitate, Simethicone, Hydrolyzed hyaluronic acid, Tetrasodium EDTA, Cetyl alcohol, Stearyl alcohol, Dipropylene glycol, Hydrolyzed rice protein, Sorbitan laurate, Polysorbate 20, T-butyl alcohol, Panax ginseng root extract, Sodium lauroyl lactylate, Phyllanthus emblica fruit extract, Carbomer, Calcium hydroxymethionine, 3-aminopropane sulfonic acid, Hydroxyethylcellulose, Potassium hydroxide, Dimethylmethoxy chromanol, Acetyl dipeptide-1 cetyl ester, Morus alba leaf extract, Ceramide NP, Ceramide AP, Sodium benzoate, Phytosphingsine, Cholesterol, Ethylhexylglycerin, Tocopherol, Palmitoyl tripeptide-1, Palmitoyl tetrapeptide-7, Ceramide EOP, CI 77891 (Titanium dioxide), CI 77491 (Iron oxides), CI 14700 (Red 4).

Description

No7 Restore & Renew FACE & NECK MULTI ACTION Anti-Ageing Skincare System

5 key age defying results for FACE & NECK:

Noticeably firmer feeling skin

Wrinkles appear visbly reduced

A more even looking skin tone

Neck looks visibly smoother and feels noticeably firmer

Younger looking skin

50 ml e 1.69 Fl.Oz.

Day Cream:

MULTI ACTION results, all day hydration for visibly younger looking skin.

Combining the protective power of SPF 30, our unique Double Defence technology and our No7 age defying ingredients.

The perfect partner to your No7 Restore & Renew MULTI ACTION serum, this day cream works to visibly reduce the appearance of 5 key signs of ageing: skin feels firmer, wrinkles appear visibly reduced, neck looks visibly smoother and feels noticeably firmer, skin is intensely moisturized.

PATIENT COUNSELING INFORMATION

USA: Questions? 1-866-75-BOOTS

Made in the UK

The Boots Company PLC

Nottingham England NG2 3AA

Dist. in the USA by Boots Retail USA Inc. New York NY 10005

www.no7beauty.com